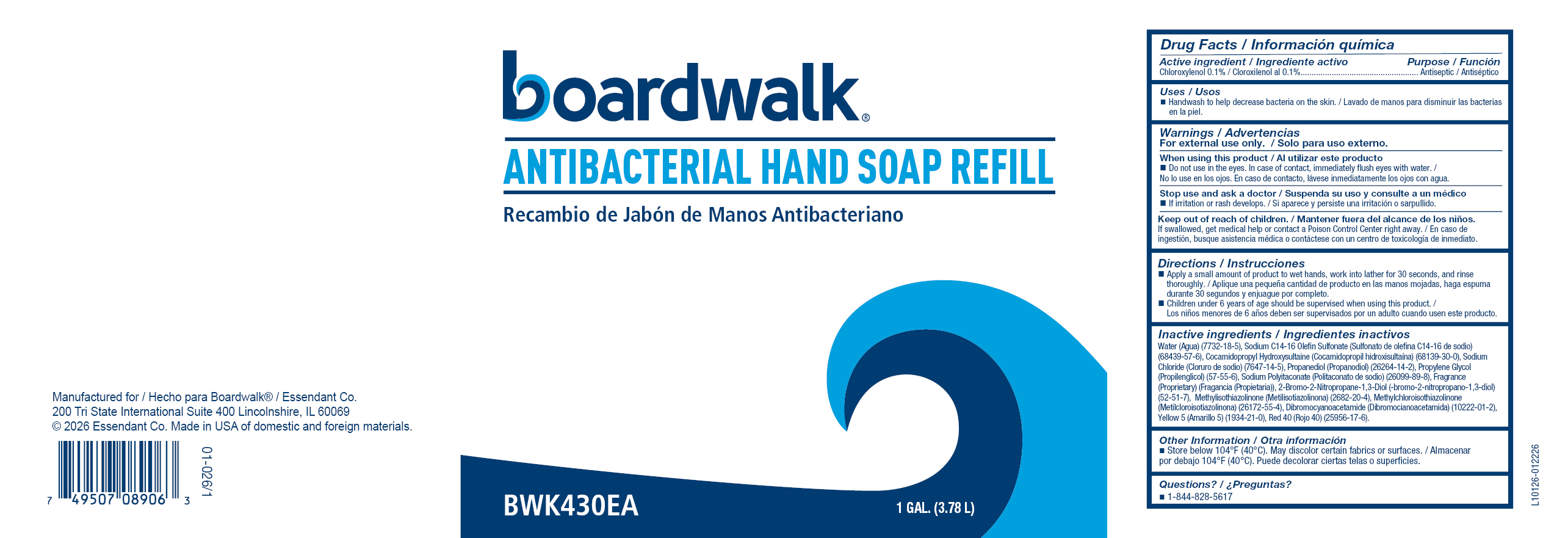 DRUG LABEL: Antibacterial Hand Refill
NDC: 71906-701 | Form: SOAP
Manufacturer: Essendant Co.
Category: otc | Type: HUMAN OTC DRUG LABEL
Date: 20260217

ACTIVE INGREDIENTS: CHLOROXYLENOL 1 g/1 L
INACTIVE INGREDIENTS: SODIUM C14-16 OLEFIN SULFONATE; PROPYLENE GLYCOL; FD&C RED NO. 40; PROPANEDIOL; METHYLCHLOROISOTHIAZOLINONE; WATER; SODIUM CHLORIDE; METHYLISOTHIAZOLINONE; FD&C YELLOW NO. 5; COCAMIDOPROPYL HYDROXYSULTAINE; SODIUM POLYITACONATE (2800 MW, PHOSPHATE TERMINATED); BRONOPOL

Active Ingredient / Ingrediente activo

Chloroxylenol 0.1% / Cloroxilenol al 0.1%

Purpose / Función

Antiseptic / Antiséptico

Uses / Usos

 Handwash to help decrease bacteria on the skin. / Lavado de manos para disminuir las bacterias en la piel.

Warnings / Advertencias

For external use only. / Solo para uso externo.

When using this product / Al utilizar este producto

 Do not use in the eyes. In case of contact, immediately flush eyes with water. / No lo use en los ojos. En caso de contacto, lávese inmediatamente los ojos con agua.

Stop use and ask a doctor / Suspenda su uso y consulte a un médico
 If irritation or rash develops. / Si aparece y persiste una irritación o sarpullido.

Keep out of reach of children. / Mantener fuera del alcance de los niños.
If swallowed, get medical help or contact a Poison Control Center right away. / En caso de ingestión, busque asistencia médica o contáctese con un centro de toxicología de inmediato.

Directions / Instrucciones

 Apply a small amount of product to wet hands, work into lather for 30 seconds, and rinse thoroughly. / Aplique una pequeña cantidad de producto en las manos mojadas, haga espuma durante 30 segundos y enjuague por completo.
 Children under 6 years of age should be supervised when using this product. / Los niños menores de 6 años deben ser supervisados por un adulto cuando usen este producto.

Inactive ingredients / Ingredientes inactivos

Water (Agua) (7732-18-5), Sodium C14-16 Olefin Sulfonate (Sulfonato de olefina C14-16 de sodio) (68439-57-6), Cocamidopropyl Hydroxysultaine (Cocamidopropil hidroxisultaína) (68139-30-0), Sodium Chloride (Cloruro de sodio) (7647-14-5), Propanediol (Propanodiol) (26264-14-2), Propylene Glycol (Propilenglicol) (57-55-6), Sodium Polyitaconate (Politaconato de sodio) (26099-89-8), Fragrance (Proprietary) (Fragancia (Propietaria)), 2-Bromo-2-Nitropropane-1,3-Diol (-bromo-2-nitropropano-1,3-diol) (52-51-7), Methylisothiazolinone (Metilisotiazolinona) (2682-20-4), Methylchloroisothiazolinone (Metilcloroisotiazolinona) (26172-55-4), Yellow 5 (Amarillo 5) (1934-21-0), Red 40 (Rojo 40) (25956-17-6).

Other Information / Otra información

 Store below 104°F (40°C). May discolor certain fabrics or surfaces. / Almacenar por debajo 104°F (40°C). Puede decolorar ciertas telas o superficies.

Questions? / ¿Preguntas?

 1-844-828-5617